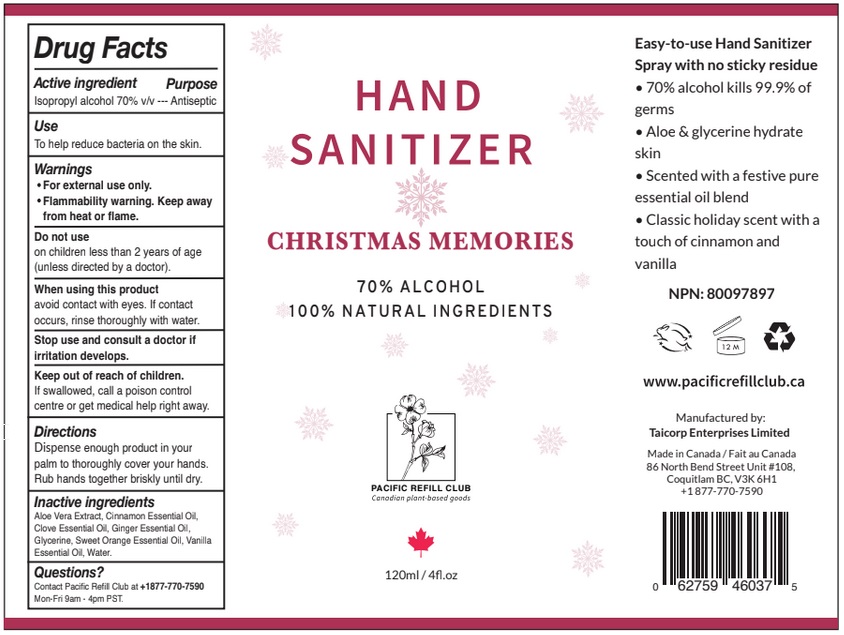 DRUG LABEL: Hand Sanitizer CHRISTMAS MEMORIES
NDC: 79883-010 | Form: SPRAY
Manufacturer: TAICORP ENTERPRISES LIMITED
Category: otc | Type: HUMAN OTC DRUG LABEL
Date: 20200825

ACTIVE INGREDIENTS: ISOPROPYL ALCOHOL 70 mL/100 mL
INACTIVE INGREDIENTS: ALOE VERA LEAF; CINNAMON OIL; CLOVE OIL; GINGER OIL; GLYCERIN; ORANGE OIL; VANILLA PLANIFOLIA OIL; WATER

Active Ingredient

Isopropyl alcohol 70% v/v

Purpose

Antiseptic

Use

To help reduce bacteria on the skin.

Warnings

- For external use only.
- Flammability warning. Keep away from heat or flame.

Do not useon children less than 2 years of age (unless directed by a doctor).

When using this product avoid contact with eyes. If contact occurs, rinse thoroughly with water.

Stop use and consult a doctor if irritation develops.

Keep out of reach of children. If swallowed, get medical help or contact a Poison Control Center right away.

Directions

- Dispense enough product in your palm to thoroughly cover your hands.
- Rub hands together briskly until dry.

Inactive ingredients

Aloe Vera Extract, Cinnamon Essential Oil, Clove Essential Oil, Ginger Essential Oil, Glycerin, Sweet Orange Essential Oil, Vanilla Essential Oil, Water.